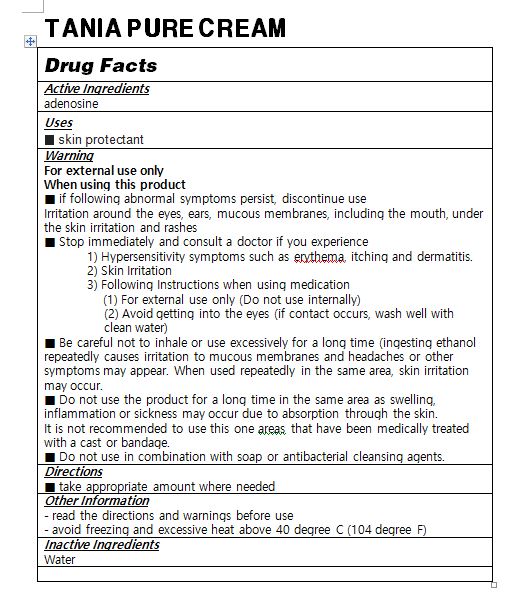 DRUG LABEL: TANIA PURECREAM
NDC: 82237-0001 | Form: CREAM
Manufacturer: NFC LIFE SCIENCE CO.,LTD
Category: otc | Type: HUMAN OTC DRUG LABEL
Date: 20231213

ACTIVE INGREDIENTS: NIACINAMIDE 2 g/100 mL
INACTIVE INGREDIENTS: GARLIC OIL

ACTIVE INGREDIENT

niacinamide

INACTIVE INGREDIENT

garlic fermented extract, etc.

PURPOSE

skin protectant

Keep out of reach of the children

INDICATIONS AND USAGE

Take a proper amount after shower apply it gently according to skin texture, and wash it off to finish

WARNINGS

1. Do not use in the following cases(Eczema and scalp wounds)
2.Side Effects
1)Due to the use of this druf if rash, irritation, itching and symptopms of hypersnesitivity occur dicontinue use and consult your phamacisr or doctor
3.General Precautions
1)If in contact with the eyes, wash out thoroughty with water If the symptoms are servere, seek medical advice immediately
2)This product is for exeternal use only. Do not use for internal use
4.Storage and handling precautions
1)If possible, avoid direct sunlight and store in cool and area of low humidity
2)In order to maintain the quality of the product and avoid misuse
3)Avoid placing the product near fire and store out in reach of children

DOSAGE AND ADMINISTRATION

for external use only